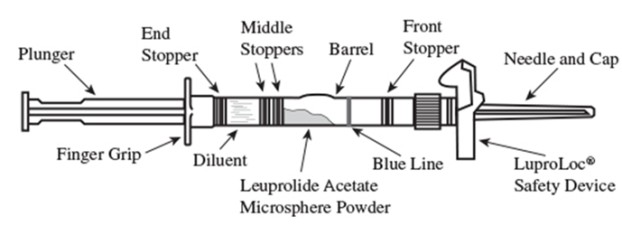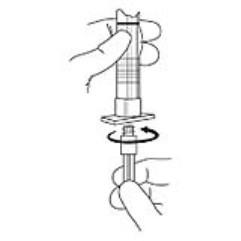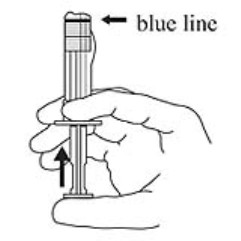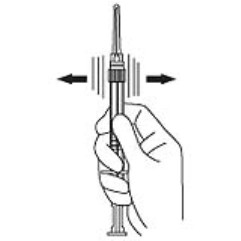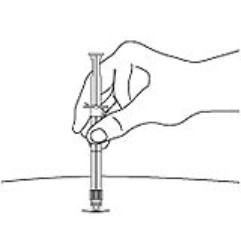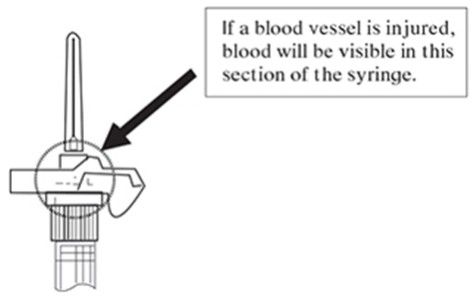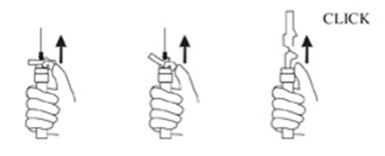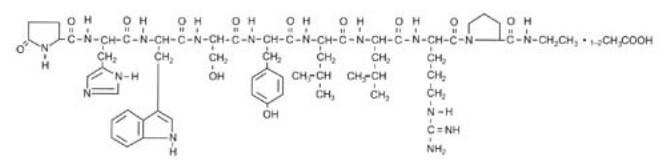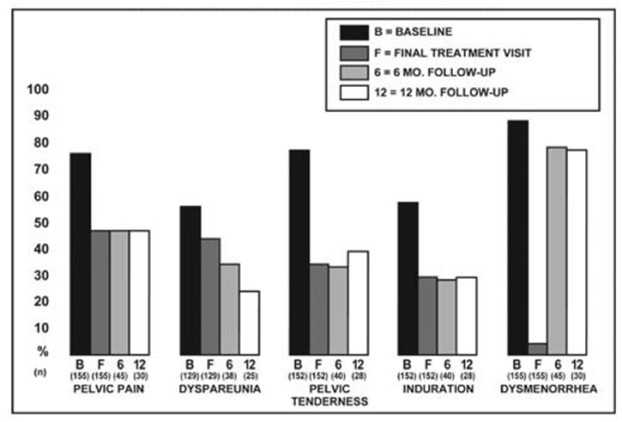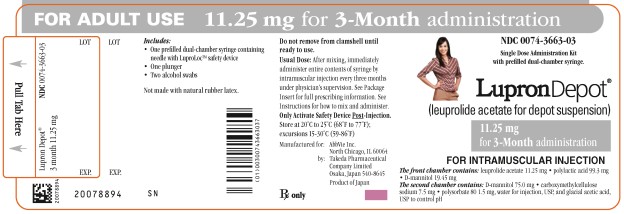 DRUG LABEL: Lupron Depot
NDC: 0074-3663 | Form: KIT | Route: INTRAMUSCULAR
Manufacturer: AbbVie Inc.
Category: prescription | Type: HUMAN PRESCRIPTION DRUG LABEL
Date: 20250910

ACTIVE INGREDIENTS: LEUPROLIDE ACETATE 11.25 mg/1.5 mL
INACTIVE INGREDIENTS: POLYLACTIDE 99.3 mg/1.5 mL; MANNITOL; CARBOXYMETHYLCELLULOSE SODIUM, UNSPECIFIED 7.5 mg/1.5 mL; POLYSORBATE 80 1.5 mg/1.5 mL; WATER; ACETIC ACID; ISOPROPYL ALCOHOL; WATER

HIGHLIGHTS OF PRESCRIBING INFORMATION

These highlights do not include all the information needed to use LUPRON DEPOT 11.25 mg safely and effectively. See full prescribing information for LUPRON DEPOT 11.25 mg.
LUPRON DEPOT 11.25 mg (leuprolide acetate for depot suspension) for injection, for intramuscular use
Initial U.S. Approval: 1985

RECENT MAJOR CHANGES

Warnings and Precautions, Severe Cutaneous Adverse Reactions (5.3) | 9/2025

1 INDICATIONS AND USAGE

LUPRON DEPOT 11.25 mg is a gonadotropin-releasing hormone (GnRH) agonist indicated for:

Endometriosis

- Management of endometriosis, including pain relief and reduction of endometriotic lesions. (1.1)
- In combination with a norethindrone acetate for initial management of the painful symptoms of endometriosis and for management of recurrence of symptoms. (1.1)

Limitations of Use:

- The total duration of therapy with LUPRON DEPOT 11.25 mg plus add-back therapy should not exceed 12 months due to concerns about adverse impact on bone mineral density. (1.1, 2.1, 5.1)

Uterine Leiomyomata (Fibroids)

- Concomitant use with iron therapy for preoperative hematologic improvement of women with anemia caused by fibroids for whom three months of hormonal suppression is deemed necessary. (1.2)

Limitations of Use:

- LUPRON DEPOT 11.25 mg is not indicated for combination use with norethindrone acetate add-back therapy for the preoperative hematologic improvement of women with anemia caused by heavy menstrual bleeding due to fibroids. (1.2)

2 DOSAGE AND ADMINISTRATION

LUPRON DEPOT 11.25mg for 3-month administration, given by a healthcare provider as a single intramuscular injection.

LUPRON DEPOT 11.25 mg has different release characteristics than LUPRON 3.75 mg and is dosed differently. (2.1)

- Do not substitute LUPRON DEPOT 11.25 mg for LUPRON DEPOT 3.75 mg.
- Do not administer LUPRON DEPOT 11.25 mg more frequently than every 3 months.
- Do not give a fractional dose of the LUPRON DEPOT 11.25 mg, as it is not equivalent to the same dose of the LUPRON DEPOT 3.75 mg monthly formulation.

Reconstitute LUPRON DEPOT 11.25 mg prior to use. (2.2)

Endometriosis:

- LUPRON DEPOT 11.25 mg administered as a single intramuscular (IM) injection once every three months for up to two injections (6 months of therapy). LUPRON DEPOT may be administered alone or in combination with daily 5 mg tablet of norethindrone acetate (add-back). (2.1)
- If endometriosis symptoms recur after initial course of therapy, retreatment for no more than six months may be considered but only with the addition of norethindrone acetate add-back therapy. Do not re-treat with LUPRON DEPOT 11.25 mg alone. (2.1)

Fibroids:

- Recommended dose of LUPRON DEPOT 11.25 mg is one IM injection. (2.1)

3 DOSAGE FORMS AND STRENGTHS

- Depot suspension for injection: 11.25 mg lyophilized powder for reconstitution in a dual-chamber syringe. (3)

4 CONTRAINDICATIONS

- Hypersensitivity to GnRH, GnRH agonist analogs, including leuprolide acetate, or any of the excipients in LUPRON DEPOT 11.25 mg. (4, 5.4)
- Undiagnosed abnormal uterine bleeding. (4)
- Pregnancy. (4, 8.1)

If LUPRON DEPOT 11.25 mg is administered with norethindrone acetate, the contraindications for norethindrone acetate also apply. (4)

5 WARNINGS AND PRECAUTIONS

- Loss of bone mineral density (BMD): Duration of treatment is limited by risk of bone mineral density. When using for management of endometriosis: combination use with norethindrone acetate is effective in reducing loss of BMD; do not retreat without combination norethindrone acetate. Assess BMD before retreatment. (1.1, 1.2, 5.1)
- Embryo-Fetal Toxicity: May cause fetal harm. Exclude pregnancy before initiating treatment if clinically indicated and discontinue use if pregnancy occurs. Use non-hormonal methods of contraception only. (5.2)
- Severe Cutaneous Adverse Reactions (SCARs), including Stevens-Johnson syndrome/toxic epidermal necrolysis (SJS/TEN), occurred in patients treated with LUPRON DEPOT. Discontinue LUPRON DEPOT 11.25 mg if signs or symptoms of SCARs develop. Permanently discontinue if SCARs are confirmed. (5.3)
- Hypersensitivity reactions including anaphylaxis, have been reported with LUPRON DEPOT 11.25 mg. (5.4)
- If LUPRON is administered with norethindrone acetate, the warnings and precautions for norethindrone acetate apply to the combination regimen. (5.8)

6 ADVERSE REACTIONS

Most common adverse reactions (>10%) in clinical trials were hot flashes/sweats, headache/migraine, vaginitis, depression/emotional lability, general pain, weight gain/loss, nausea/vomiting, decreased libido, and dizziness. (6.1)

To report SUSPECTED ADVERSE REACTIONS, contact AbbVie Inc. at 1-800-633-9110 or FDA at 1-800-FDA-1088 or www.fda.gov/medwatch

FULL PRESCRIBING INFORMATION

1 INDICATIONS AND USAGE

1.1 Endometriosis

Monotherapy

LUPRON DEPOT 11.25 mg is indicated for management of endometriosis, including pain relief and reduction of endometriotic lesions.

In Combination with Norethindrone Acetate

LUPRON DEPOT 11.25 mg in combination with norethindrone acetate is indicated for initial management of the painful symptoms of endometriosis and for management of recurrence of symptoms.

Use of norethindrone acetate in combination with LUPRON DEPOT 11.25 mg is referred to as add-back therapy, and is intended to reduce the loss of bone mineral density (BMD) and reduce vasomotor symptoms associated with use of LUPRON DEPOT 11.25 mg.

Limitations of Use:

The total duration of therapy with LUPRON DEPOT 11.25 mg plus add-back therapy should not exceed 12 months due to concerns about adverse impact on bone mineral density [see Dosage and Administration (2.1) and Warnings and Precautions (5.1)].

1.2 Uterine Leiomyomata (Fibroids)

LUPRON DEPOT 11.25 mg, used concomitantly with iron therapy, is indicated for the preoperative hematologic improvement of women with anemia caused by fibroids for whom three months of hormonal suppression is deemed necessary.

Consider a one-month trial period on iron alone, as some women will respond to iron alone [see Clinical Studies (14.2)]. LUPRON DEPOT 11.25 mg may be added if the response to iron alone is considered inadequate.

Limitations of Use:

LUPRON DEPOT 11.25 mg is not indicated for combination use with norethindrone acetate add-back therapy for the preoperative hematologic improvement of women with anemia caused by heavy menstrual bleeding due to fibroids [see Dosage and Administration (2.1)].

2 DOSAGE AND ADMINISTRATION

2.1 Important Use Information

LUPRON DEPOT 11.25 mg must be administered by a healthcare professional.

LUPRON DEPOT 11.25 mg for 3-month administration has different release characteristics than LUPRON 3.75 mg for 1-month administration and is dosed differently.

- Do not substitute LUPRON DEPOT 11.25 mg for LUPRON DEPOT 3.75 mg.
- Do not administer LUPRON DEPOT 11.25 mg more frequently than every 3 months.
- Do not give a fractional dose of the LUPRON DEPOT 11.25 mg, as it is not equivalent to the same dose of the LUPRON DEPOT 3.75 mg monthly formulation.

Endometriosis

The initial and retreatment dosage regimens for LUPRON DEPOT 11.25 mg for the management of women with endometriosis are outlined in Table 1.

Table 1. LUPRON DEPOT 11.25 mg, Management of Endometriosis
Treatment Phase | LUPRON DEPOT 11.25 mg Dosing | Maximum Treatment Duration
Initial Treatment^1 | 11.25 mg IM every 3 months for 1 to 2 doses | 6 months
Retreatment^2 | 11.25 mg IM every 3 months for 1 to 2 doses | 6 months
 |  | 12 MONTHS^3 TOTAL TREATMENT DURATION

^1May use LUPRON DEPOT 11.25 mg with or without norethindrone acetate 5 mg tablet taken daily.

^2Use LUPRON DEPOT 11.25 mg with norethindrone acetate for retreatment 5 mg tablet taken daily [see Warnings and Precautions (5.1)] and assess bone mineral density (BMD) prior to retreatment.

^3Treatment should not exceed 12 months due to concerns about adverse impact on bone mineral density.

Fibroids

The recommended dosage of LUPRON DEPOT 11.25 mg is one IM injection of 11.25 mg which provides a three-month treatment course.

2.2 Reconstitution and Administration for Injection of LUPRON DEPOT

- Reconstitute and administer the lyophilized microsphere as a single IM injection as directed below. Visually inspect the drug product for particulate matter and discoloration prior to administration, whenever solution and container permit.
- Inject the LUPRON DEPOT 11.25 mg suspension immediately or discard if not used within two hours as the suspension does not contain a preservative.

1. Visually inspect the LUPRON DEPOT 11.25 mg powder. Do not use the syringe if clumping or caking is evident. A thin layer of powder on the wall of the syringe is considered normal prior to mixing with the diluent. The diluent should appear clear.

2. To prepare for injection, screw the white plunger into the end stopper until the stopper begins to turn (see Figure A and Figure B).

Figure A:

Figure B:

3. Hold the syringe UPRIGHT. Release the diluent by SLOWLY PUSHING the plunger for 6 to 8 seconds until the first middle stopper is at the blue line in the middle of the barrel (see Figure C).

Figure C:

4. Keep the syringe upright. Mix the microsphere powder thoroughly by gently shaking the syringe until the powder forms a uniform suspension. The suspension will appear milky. If the powder adheres to the stopper or caking/clumping is present, tap the syringe with your finger to disperse. Do not use if any of the powder has not gone into suspension (see Figure D).

Figure D:

5. Keep the syringe upright. With the opposite hand pull the needle cap upward without twisting.

6. Keep the syringe upright. Advance the plunger to expel the air from the syringe. The syringe is now ready for injection.

7. After cleaning the injection site with an alcohol swab, administer the IM injection by inserting the needle at a 90-degree angle into the gluteal area, anterior thigh, or deltoid. Injection sites should be alternated (see Figure E).

Figure E:

Note: If a blood vessel is accidentally penetrated, aspirated blood will be visible just below the luer lock (see Figure F) and can be seen through the transparent LuproLoc® safety device. If blood is present, remove the needle immediately. Do not inject the medication.

Figure F:

8. Inject the entire contents of the syringe intramuscularly.

9. Withdraw the needle. Once the syringe has been withdrawn, immediately activate the LuproLoc® safety device by pushing the arrow on the lock upward towards the needle tip with the thumb or finger, as illustrated, until the needle cover of the safety device over the needle is fully extended and a click is heard or felt (see Figure G).

Figure G:

10. Dispose of the syringe according to local regulations/procedures.

3 DOSAGE FORMS AND STRENGTHS

For Injection: 11.25 mg of leuprolide acetate as a white lyophilized microsphere powder for reconstitution in a single dose prefilled dual chamber syringe; with one chamber containing the lyophilized powder and the other chamber containing the clear diluent.

4 CONTRAINDICATIONS

LUPRON DEPOT 11.25 mg is contraindicated in women with the following:

- Hypersensitivity to gonadotropin-releasing hormone (GnRH), GnRH agonist analogs, including leuprolide acetate, or any of the excipients in LUPRON DEPOT 11.25 mg [see Warnings and Precautions (5.4) and Adverse Reactions (6.2)]
- Undiagnosed abnormal uterine bleeding
- Pregnancy [see Warnings and Precautions (5.2) and Use in Specific Populations (8.1)]

When norethindrone acetate is administered with LUPRON DEPOT 11.25 mg, the contraindications to the use of norethindrone acetate also apply to this combination regimen. Refer to the norethindrone acetate prescribing information for a list of contraindications for norethindrone acetate.

5 WARNINGS AND PRECAUTIONS

5.1 Loss of Bone Mineral Density

LUPRON DEPOT 11.25 mg induces a hypoestrogenic state that results in loss of bone mineral density (BMD), some of which may not be reversible after stopping treatment. In women with major risk factors for decreased BMD such as chronic alcohol use (> 3 units per day), tobacco use, strong family history of osteoporosis, or chronic use of drugs that can decrease BMD, such as anticonvulsants or corticosteroids, use of LUPRON DEPOT 11.25 mg may pose an additional risk. Carefully weigh the risks and benefits of LUPRON DEPOT 11.25 mg use in these populations.

The duration of LUPRON DEPOT 11.25 mg treatment is limited by the risk of loss of bone mineral density [see Dosage and Administration (2.1)].

When using LUPRON DEPOT 11.25 mg for the management of endometriosis, combination use of norethindrone acetate (add-back therapy) is effective in reducing the loss of BMD that occurs with leuprolide acetate [see Clinical Studies (14.2)]. Do not retreat with LUPRON DEPOT 11.25 mg without combination norethindrone acetate. Assess BMD before retreatment.

5.2 Embryo-Fetal Toxicity

Based on animal reproduction studies and the drug’s mechanism of action, LUPRON DEPOT 11.25 mg may cause fetal harm if administered to a pregnant woman and is contraindicated in pregnant women. Exclude pregnancy prior to initiating treatment with LUPRON DEPOT 11.25 mg if clinically indicated. Discontinue LUPRON DEPOT 11.25 mg if the woman becomes pregnant during treatment and inform the woman of potential risk to the fetus [see Contraindications (4) and Use in Specific Populations (8.1)]. Advise women to notify their healthcare provider if they believe they may be pregnant.

When used at the recommended dose and dosing interval, LUPRON DEPOT 11.25 mg usually inhibits ovulation and stops menstruation. Contraception, however, is not ensured by taking LUPRON DEPOT 11.25 mg. If contraception is indicated, advise women to use non-hormonal methods of contraception while on treatment with LUPRON DEPOT 11.25 mg.

5.3 Severe Cutaneous Adverse Reactions

Severe cutaneous adverse reactions (SCARs) have been reported in patients receiving GnRH agonists, including LUPRON DEPOT. These reactions include Stevens-Johnson syndrome/toxic epidermal necrolysis (SJS/TEN), drug reaction with eosinophilia and systemic symptoms (DRESS), and acute generalized exanthematous pustulosis (AGEP), including cases with visceral involvement and/or requiring skin grafts [see Adverse Reactions (6.2)].

Monitor patients for the signs and symptoms of SCARs such as fever, flu-like symptoms, mucosal lesions, progressive skin rash, or lymphadenopathy. Advise patients of the signs and symptoms of SCARs.

If a SCAR is suspected, discontinue LUPRON DEPOT 11.25 mg. Consult with a healthcare provider with expertise in the diagnosis and management of SCARs. If a diagnosis of SCAR is confirmed, permanently discontinue LUPRON DEPOT 11.25 mg.

5.4 Hypersensitivity Reactions

Hypersensitivity reactions, including anaphylaxis, have been reported with LUPRON DEPOT use. LUPRON DEPOT 11.25 mg is contraindicated in women with a history of hypersensitivity to gonadotropin-releasing hormone (GnRH) or GnRH agonist analogs [see Adverse Reactions (6.2)].

In clinical trials of LUPRON DEPOT 11.25 mg, adverse events of asthma were reported in women with pre-existing histories of asthma, sinusitis, and environmental or drug allergies. Symptoms consistent with an anaphylactoid or asthmatic process have been reported postmarketing.

5.5 Initial Flare of Symptoms

Following the first dose of LUPRON DEPOT 11.25 mg, sex steroids temporarily rise above baseline because of the physiologic effect of the drug. Therefore, an increase in symptoms may be observed during the initial days of therapy, but these should dissipate with continued therapy.

5.6 Convulsions

There have been postmarketing reports of convulsions in women on GnRH agonists, including leuprolide acetate. These included women with and without concurrent medications and comorbid conditions.

5.7 Clinical Depression

Depression may occur or worsen during treatment with GnRH agonists including LUPRON DEPOT 11.25 mg [see Adverse Reactions (6.1)]. Carefully observe women for depression, especially those with a history of depression and consider whether the risks of continuing LUPRON DEPOT 11.25 mg outweigh the benefits. Women with new or worsening depression should be referred to a mental health professional, as appropriate.

5.8 Risks Associated with Norethindrone Combination Treatment

If LUPRON DEPOT 11.25 mg is administered with norethindrone acetate, the warnings and precautions for norethindrone acetate apply to this regimen. Refer to the norethindrone acetate prescribing information for a full list of the warnings and precautions for norethindrone acetate.

6 ADVERSE REACTIONS

The following clinically significant adverse reactions are described elsewhere in the labeling:

- Loss of Bone Mineral Density [see Warnings and Precautions (5.1)]
- Severe Cutaneous Adverse Reactions [see Warnings and Precautions (5.3)]
- Hypersensitivity Reactions [see Warnings and Precautions (5.4)]
- Initial Flare of Symptoms with Management of Endometriosis [see Warnings and Precautions (5.5)]
- Convulsions [see Warnings and Precautions (5.6)]
- Clinical Depression [see Warnings and Precautions (5.7)]

6.1 Clinical Trials Experience

Because clinical trials are conducted under widely varying conditions, adverse reaction rates observed in the clinical trials of a drug cannot be directly compared to rates in the clinical trials of another drug and may not reflect the rates observed in clinical practice.

LUPRON DEPOT 11.25 mg (Monotherapy)

The safety of LUPRON DEPOT 11.25 mg for the endometriosis and fibroids indications was established based on adequate and well-controlled adult studies of LUPRON DEPOT 3.75 mg for 1-month administration and on a single trial of LUPRON DEPOT 11.25 mg. The safety of LUPRON DEPOT 3.75 mg was evaluated in six clinical studies in which a total of 332 women were treated for up to six months. Women were treated with monthly IM injections of LUPRON DEPOT 3.75 mg. The population age range was 18 to 53 years old.

Adverse Reactions (>1%) Leading to Study Discontinuation

In the six studies 1.8% of women treated with LUPRON DEPOT 3.75 mg discontinued prematurely due to hot flashes.

Common Adverse Reactions

The safety of LUPRON DEPOT 3.75 mg was evaluated in controlled clinical trials in 166 women with endometriosis and 166 women with uterine fibroids. Adverse reactions reported in ≥ 5% of women in either of these populations are noted in Tables 2 and 3, below.

Table 2. Adverse Reactions Reported in ≥ 5% of Women with Endometriosis Taking LUPRON DEPOT 3.75 mg - 2 Studies
 | LUPRON DEPOT 3.75 mg N=166 | Danazol N=136 | Placebo N=31
 | % | % | %
Hot flashes/sweats* | 84 | 57 | 29
Headache* | 32 | 22 | 6
Vaginitis* | 28 | 17 | 0
Depression/emotional lability* | 22 | 20 | 3
General pain | 19 | 16 | 3
Weight gain/loss | 13 | 26 | 0
Nausea/vomiting | 13 | 13 | 3
Decreased libido* | 11 | 4 | 0
Dizziness | 11 | 3 | 0
Acne | 10 | 20 | 0
Skin reactions | 10 | 15 | 3
Joint disorder* | 8 | 8 | 0
Edema | 7 | 13 | 3
Paresthesias | 7 | 8 | 0
GI disturbances* | 7 | 6 | 3
Neuromuscular disorders* | 7 | 13 | 0
Breast changes/tenderness/pain* | 6 | 9 | 0
Nervousness* | 5 | 8 | 0
In these same studies, symptoms reported in < 5% of women included:
- Body as a Whole - Injection site reactions
- Cardiovascular System - Palpitations, syncope, tachycardia
- Digestive System - Appetite changes, dry mouth, thirst
- Endocrine System - Androgen-like effects, lactation
- Blood and Lymphatic System - Ecchymosis
- Nervous/Psychiatric System - Anxiety*, insomnia/sleep disorders*, delusions, memory disorder, personality disorder
- Dermal System - Alopecia, hair disorder
- Ocular system - Ophthalmologic disorders*
- Urogenital System - Dysuria*.
  * = Possible effect of decreased estrogen.

Table 3. Adverse Reactions Reported in ≥ 5% of Women with Uterine Fibroids (4 Studies) Taking LUPRON DEPOT 3.75 mg
 | LUPRON DEPOT 3.75 mg N=166 | Placebo N=163
 | % | %
Hot flashes/sweats* | 73 | 18
Headache* | 26 | 18
Vaginitis* | 11 | 2
Depression/emotional lability* | 11 | 4
Asthenia | 8 | 5
General pain | 8 | 6
Joint disorder* | 8 | 3
Edema | 5 | 1
Nausea/vomiting | 5 | 4
Nervousness* | 5 | 1
In these same studies, symptoms reported in < 5% of women included:
- Body as a Whole - Body odor, flu syndrome, injection site reactions
- Cardiovascular System - Tachycardia
- Digestive System - Appetite changes, dry mouth, taste perversion
- Endocrine System - Androgen-like effects, menstrual disorders
- Nervous/Psychiatric System - Anxiety*, insomnia/sleep disorders*
- Respiratory System - Rhinitis
- Dermal System - Nail disorder
- Ocular system - Conjunctivitis
  * = Possible effect of decreased estrogen.

In one controlled clinical trial utilizing the monthly formulation of LUPRON DEPOT 3.75 mg and LUPRON DEPOT 7.5 mg in women diagnosed with uterine fibroids received one injection every 4 weeks for a duration of 12 weeks. Adverse reactions of galactorrhea, pyelonephritis, and urinary incontinence were reported in the 7.5 mg dose group but not in the 3.75 mg dose group. Generally, a higher incidence of hypoestrogenic effects was observed at the higher dose.

In a pharmacokinetic trial involving 20 healthy female subjects receiving LUPRON DEPOT 11.25 mg, a few adverse reactions were reported with this formulation that were not reported previously, including face edema.

In a phase 4 study involving women with endometriosis who received LUPRON DEPOT 3.75 mg (N=20) administered monthly or LUPRON DEPOT 11.25 mg (N=21) administered every 3 months, similar adverse reactions were reported by the two groups of women. In general, the safety profiles of the two formulations were comparable in this study.

LUPRON DEPOT 3.75 mg in combination with Norethindrone Acetate 5 mg

The safety of co-administering LUPRON DEPOT 3.75 mg and norethindrone acetate was evaluated in two clinical studies in which a total of 242 women with endometriosis were treated for up to one year. Women were treated with monthly IM injections of LUPRON DEPOT 3.75 mg (13 injections) alone or monthly IM injections of LUPRON DEPOT 3.75 mg (13 injections) plus norethindrone acetate 5 mg daily. The population age range was 17 to 43 years old. The majority of women were Caucasian (87%).

In one study, 106 women were randomized to one year of treatment with LUPRON DEPOT 3.75 mg alone or with LUPRON DEPOT 3.75 mg and norethindrone acetate. The other study was an open-label, single arm clinical study in 136 women on one year of treatment with LUPRON DEPOT 3.75 mg plus norethindrone acetate, with follow-up for up to 12 months after completing treatment.

Adverse Reactions (>1%) Leading to Study Discontinuation

In the controlled study, 18% of women treated monthly with LUPRON DEPOT 3.75 mg and 18% of women treated monthly with LUPRON DEPOT 3.75 mg plus norethindrone acetate discontinued therapy due to adverse reactions, most commonly hot flashes (6%) and insomnia (4%) in the LUPRON DEPOT 3.75 mg alone group and hot flashes and emotional lability (4% each) in the LUPRON DEPOT 3.75 mg plus norethindrone group.

In the open-label study, 13% of women treated monthly with LUPRON DEPOT 3.75 mg plus norethindrone acetate discontinued therapy due to adverse reactions, most commonly depression (4%) and acne (2%).

Common Adverse Reactions

Table 4 lists the adverse reactions observed in at least 5% of women in any treatment group, during the first 6 months of treatment in the two add-back clinical studies, in which women were treated with monthly LUPRON DEPOT 3.75 mg with or without norethindrone acetate 5mg daily co-treatment. The most frequently-occurring adverse reactions observed in these studies were hot flashes and headaches.

Table 4. Adverse Reactions Occurring in the First Six Months of Treatment in ≥ 5% of Women with Endometriosis
 | Controlled Study |  | Open Label Study
 | LD-Only* | LD/N† | LD/N†
 | N=51 | N=55 | N=136
Adverse Reactions | % | % | %
Any Adverse Reaction | 98 | 96 | 93
Hot flashes/Sweats | 98 | 87 | 57
Headache/Migraine | 65 | 51 | 46
Depression/Emotional Lability | 31 | 27 | 34
Insomnia/Sleep Disorder | 31 | 13 | 15
Nausea/Vomiting | 25 | 29 | 13
Pain | 24 | 29 | 21
Vaginitis | 20 | 15 | 8
Asthenia | 18 | 18 | 11
Dizziness/Vertigo | 16 | 11 | 7
Altered Bowel Function (constipation, diarrhea) | 14 | 15 | 10
Weight Gain | 12 | 13 | 4
Decreased Libido | 10 | 4 | 7
Nervousness/Anxiety | 8 | 4 | 11
Breast Changes/Pain/Tenderness | 6 | 13 | 8
Memory Disorder | 6 | 2 | 4
Skin/Mucous Membrane Reaction | 4 | 9 | 11
GI Disturbance (dyspepsia, flatulence) | 4 | 7 | 4
Androgen-Like Effects (acne, alopecia) | 4 | 5 | 18
Changes in Appetite | 4 | 0 | 6
Injection Site Reaction | 2 | 9 | 3
Neuromuscular Disorder (leg cramps, paresthesia) | 2 | 9 | 3
Menstrual Disorders | 2 | 0 | 5
Edema | 0 | 9 | 7
* LD-Only = LUPRON DEPOT 3.75 mg
† LD/N = LUPRON DEPOT 3.75 mg plus norethindrone acetate 5 mg

In the controlled clinical trial, 50 of 51 (98%) women in the LUPRON DEPOT 3.75 mg arm and 48 of 55 (87%) women in the LUPRON DEPOT 3.75 mg plus norethindrone acetate arm reported experiencing hot flashes on one or more occasions during treatment.

Table 5 presents hot flash data in the last month of treatment.

Table 5. Hot Flashes in the Month Prior to the Assessment Visit (Controlled Study)
Assessment Visit | Treatment Group | Number of Women Reporting Hot Flashes |  | Number of Days with Hot Flashes |  | Maximum Number Hot Flashes in 24 Hours
 |  | N | (%) | N^2 | Mean | N^2 | Mean
Week 24 | LD-Only* | 32/37 | 86 | 37 | 19 | 36 | 5.8
 | LD/N† | 22/38 | 58^1 | 38 | 7^1 | 38 | 1.9^1
* LD-Only = LUPRON DEPOT 3.75 mg.
† LD/N = LUPRON DEPOT 3.75 mg plus norethindrone acetate 5 mg.
^1Statistically significantly less than the LD-Only group (p<0.01).
^2Number of women assessed.

Serious Adverse Reactions

Urinary tract infection (1.9%), renal calculus (0.7%), depression (0.7%)

Changes in Laboratory Values during Treatment

Liver Enzymes

Three percent of women with uterine fibroids treated with LUPRON DEPOT 3.75 mg for 1-month administration, manifested post-treatment transaminase values that were at least twice the baseline value and above the upper limit of the normal range.

In the two clinical trials of women with endometriosis, 2% (4 of 191) women receiving leuprolide acetate plus norethindrone acetate for up to 12 months developed an elevated (at least twice the upper limit of normal) SGPT and 1% (2 of 136) developed an elevated GGT. Among these six women with increased liver tests, the increases in five were observed beyond 6 months of treatment. None were associated with an elevated bilirubin concentration.

Lipids

Triglycerides were increased above the upper limit of normal in 12% of the women with endometriosis who received LUPRON DEPOT 3.75 mg and in 32% of the women receiving LUPRON DEPOT 11.25 mg.

Of those endometriosis and women with uterine fibroid whose pretreatment cholesterol values were in the normal range, mean change following therapy was +16 mg/dL to +17 mg/dL in women with endometriosis and +11 mg/dL to +29 mg/dL in women with uterine fibroids. In the women with endometriosis, increases from the pretreatment values were statistically significant (p<0.03). There was essentially no increase in the LDL/HDL ratio in women from either population receiving LUPRON DEPOT 3.75 mg.

Percent changes from baseline for serum lipids and percentages of women with serum lipid values outside of the normal range in the two studies of LUPRON DEPOT 3.75 mg and norethindrone acetate are summarized in Table 6 and Table 7 below. The major impact of adding norethindrone acetate to treatment with LUPRON DEPOT 3.75 mg was a decrease in serum HDL cholesterol and an increase in the LDL/HDL ratio.

Table 6. Serum Lipids: Mean Percent Changes from Baseline Values at Treatment Week 24
 | LUPRON DEPOT 3.75 mg |  | LUPRON DEPOT 3.75 mg plus norethindrone acetate 5 mg daily
 | Controlled Study (n=39) |  | Controlled Study (n=41) |  | Open Label Study (n=117)
 | Baseline Value* | Week 24 % Change | Baseline Value* | Week 24 % Change | Baseline Value* | Week 24 % Change
Total Cholesterol | 170.5 | 9.2% | 179.3 | 0.2% | 181.2 | 2.8%
HDL Cholesterol | 52.4 | 7.4% | 51.8 | -18.8% | 51.0 | -14.6%
LDL Cholesterol | 96.6 | 10.9% | 101.5 | 14.1% | 109.1 | 13.1%
LDL/HDL Ratio | 2.0† | 5.0% | 2.1† | 43.4% | 2.3† | 39.4%
Triglycerides | 107.8 | 17.5% | 130.2 | 9.5% | 105.4 | 13.8%
* mg/dL
† ratio

Changes from baseline tended to be greater at Week 52. After treatment, mean serum lipid levels from women with follow-up data returned to pretreatment values.

Table 7. Percentage of Women with Serum Lipids Values Outside of the Normal Range
 | LUPRON DEPOT 3.75 mg |  | LUPRON DEPOT 3.75 mg plus norethindrone acetate 5 mg daily
 | Controlled Study (n=39) |  | Controlled Study (n=41) |  | Open Label Study (n=117)
 | Week 0 | Week 24* | Week 0 | Week 24* | Week 0 | Week 24*
Total Cholesterol (>240 mg/dL) | 15% | 23% | 15% | 20% | 6% | 7%
HDL Cholesterol (<40 mg/dL) | 15% | 10% | 15% | 44% | 15% | 41%
LDL Cholesterol (>160 mg/dL) | 0% | 8% | 5% | 7% | 9% | 11%
LDL/HDL Ratio (>4.0) | 0% | 3% | 2% | 15% | 7% | 21%
Triglycerides (>200 mg/dL) | 13% | 13% | 12% | 10% | 5% | 9%
* Includes all women regardless of baseline value.

6.2 Postmarketing Experience

The following adverse reactions have been identified during post-approval use of LUPRON DEPOT monotherapy or LUPRON DEPOT with norethindrone acetate add-back therapy. Because these reactions are reported voluntarily from a population of uncertain size, it is not always possible to reliably estimate their frequency or establish a causal relationship to drug exposure.

During postmarketing surveillance which includes other dosage forms and other populations, the following adverse reactions were reported:

- Skin and Subcutaneous Tissue: rash, urticaria, photosensitivity, erythema multiforme, bullous dermatitis, dermatitis exfoliative, drug reaction with eosinophilia and systemic symptoms (DRESS), Stevens-Johnson syndrome/toxic epidermal necrolysis (SJS/TEN), and acute generalized exanthematous pustulosis (AGEP).
- Body as a whole: Hypersensitivity reactions including anaphylaxis
- Nervous/Psychiatric System: Mood swings, including depression; suicidal ideation and attempt; convulsion, peripheral neuropathy, paralysis
- Hepato-biliary system: Serious liver injury
- General disorders and administration site conditions: Injection site reactions including induration, abscess, and necrosis
- Injury, poisoning and procedural complications: Spinal fracture
- Investigations: Decreased white blood count
- Musculoskeletal and connective tissue system: Tenosynovitis-like symptoms
- Vascular system: Hypotension, hypertension, deep vein thrombosis, pulmonary embolism, myocardial infarction, stroke, transient ischemic attack
- Respiratory system: Symptoms consistent with an asthmatic process
- Multi-system disorders: Symptoms consistent with fibromyalgia (e.g., joint and muscle pain, headaches, sleep disorders, gastrointestinal distress, and shortness of breath), individually and collectively.

Pituitary apoplexy

During postmarketing surveillance, cases of pituitary apoplexy (a clinical syndrome secondary to infarction of the pituitary gland) have been reported after the administration of leuprolide acetate and other GnRH agonists. In a majority of these cases, a pituitary adenoma was diagnosed, with a majority of pituitary apoplexy cases occurring within 2 weeks of the first dose, and some within the first hour. In these cases, pituitary apoplexy has presented as sudden headache, vomiting, visual changes, ophthalmoplegia, altered mental status, and sometimes cardiovascular collapse. Immediate medical attention has been required.

7 DRUG INTERACTIONS

No drug-drug interaction studies have been conducted with LUPRON DEPOT 11.25 mg.

8 USE IN SPECIFIC POPULATIONS

8.1 Pregnancy

Risk Summary

LUPRON DEPOT 11.25 mg is contraindicated in pregnancy [see Contraindications (4)].

LUPRON DEPOT 11.25 mg may cause fetal harm based on findings from animal studies and the drug’s mechanism of action [see Clinical Pharmacology (12.1)]. There are limited human data on the use of LUPRON DEPOT in pregnant women. Based on animal reproduction studies, LUPRON DEPOT 11.25 mg may be associated with an increased risk of pregnancy complications, including early pregnancy loss and fetal harm. In animal reproduction studies, subcutaneous administration of leuprolide acetate to rabbits during the period of organogenesis caused embryo-fetal toxicity, decreased fetal weights and a dose-dependent increase in major fetal abnormalities in animals at doses less than the recommended human dose based on body surface area using an estimated daily dose. A similar rat study also showed increased fetal mortality and decreased fetal weights but no major fetal abnormalities at doses less than the recommended human dose based on body surface area using an estimated daily dose [see Data].

Data

Animal Data

When administered on day 6 of pregnancy at test dosages of 0.00024 mg/kg, 0.0024 mg/kg, and 0.024 mg/kg (1/300 to 1/3 of the human dose) to rabbits, leuprolide acetate produced a dose-related increase in major fetal abnormalities. Similar studies in rats failed to demonstrate an increase in fetal malformations. There was increased fetal mortality and decreased fetal weights with the two higher doses of LUPRON DEPOT in rabbits and with the highest dose (0.024 mg/kg) in rats.

8.2 Lactation

Risk Summary

There are no data on the presence of leuprolide acetate in either animal or human milk, the effects on the breastfed infants, or the effects on milk production.

The developmental and health benefits of breastfeeding should be considered along with the mother’s clinical need for LUPRON DEPOT 11.25 mg and any potential adverse effects on the breastfed infant from LUPRON DEPOT 11.25 mg or from the underlying maternal condition.

8.3 Females and Males of Reproductive Potential

Pregnancy Testing

Exclude pregnancy in women of reproductive potential prior to initiating LUPRON DEPOT 11.25 mg if clinically indicated [see Warnings and Precautions (5.2)].

Contraception

Females

LUPRON DEPOT 11.25 mg may cause embryo-fetal harm when administered during pregnancy. LUPRON DEPOT 11.25 mg is not a contraceptive. If contraception is indicated, advise females of reproductive potential to use a non-hormonal method of contraception during treatment with LUPRON DEPOT 11.25 mg [see Warnings and Precautions (5.2)].

Infertility

Based on its pharmacodynamic effects of decreasing secretion of gonadal steroids, fertility is expected to be decreased while on treatment with LUPRON DEPOT 11.25 mg. Clinical and pharmacologic studies in adults (>18 years) with leuprolide acetate and similar analogs have shown reversibility of fertility suppression when the drug is discontinued after continuous administration for periods of up to 24 weeks [see Clinical Pharmacology (12.1)].

There is no evidence that pregnancy rates are affected following discontinuation of LUPRON DEPOT 11.25 mg.

Animal studies (prepubertal and adult rats and monkeys) with leuprolide acetate and other GnRH analogs have shown functional recovery of fertility suppression.

8.4 Pediatric Use

Safety and effectiveness of LUPRON DEPOT 11.25 mg for management of endometriosis and the preoperative hematologic improvement of women with anemia caused by fibroids have been established in females of reproductive age. Efficacy is expected to be the same for postpubertal adolescents under the age of 18 as for users 18 years and older. The safety and effectiveness of LUPRON DEPOT 11.25 mg for these indications have not been established in premenarcheal pediatric patients.

8.5 Geriatric Use

LUPRON DEPOT 11.25 mg is not indicated in postmenopausal women and has not been studied in this population.

11 DESCRIPTION

Leuprolide acetate is a synthetic nonapeptide analog of gonadotropin-releasing hormone [GnRH or luteinizing hormone releasing hormone (LH-RH)], a GnRH agonist. The chemical name is 5- oxo-L-prolyl-L-histidyl-L-tryptophyl-L-seryl-L-tyrosyl-D-leucyl-L-leucyl-L-arginyl-N-ethyl-L-prolinamide acetate (salt) with the following structural formula:

LUPRON DEPOT 11.25 mg (leuprolide acetate for depot suspension for injection) is available in a prefilled dual-chamber syringe containing sterile lyophilized microspheres powder which, when mixed with diluent, become a suspension intended as an IM injection.

The front chamber of LUPRON DEPOT 11.25 mg prefilled dual-chamber syringe contains leuprolide acetate for depot suspension (11.25 mg), polylactic acid (99.3 mg) and D-mannitol (19.45 mg). The second chamber of diluent contains carboxymethylcellulose sodium (7.5 mg), D-mannitol (75.0 mg), polysorbate 80 (1.5 mg), water for injection, USP, and glacial acetic acid, USP to control pH.

During the manufacture of LUPRON DEPOT 11.25 mg, acetic acid is lost, leaving the peptide.

12 CLINICAL PHARMACOLOGY

12.1 Mechanism of Action

Leuprolide acetate is a long-acting GnRH analog. A single injection of LUPRON DEPOT 11.25 mg results in an initial stimulation followed by a prolonged suppression of pituitary gonadotropins. Repeated dosing of LUPRON DEPOT 11.25 mg at quarterly intervals results in decreased secretion of gonadal steroids. Consequently, tissues and functions that depend on gonadal steroids for their maintenance become quiescent. This effect is reversible on discontinuation of drug therapy.

Leuprolide acetate is not active when given orally.

12.2 Pharmacodynamics

In a pharmacokinetic/pharmacodynamic study of LUPRON DEPOT 11.25 mg in healthy female subjects (N=20), the onset of estradiol suppression was observed for individual subjects between day 4 and week 4 after dosing. By the third week following the injection, the mean estradiol concentration (8 pg/mL) was in the menopausal range. Throughout the remainder of the dosing period, mean serum estradiol levels ranged from the menopausal to the early follicular range.

Serum estradiol was suppressed to ≤20 pg/mL in all subjects within four weeks and remained suppressed (≤40 pg/mL) in 80% of subjects until the end of the 12-week dosing interval, at which time two of these subjects had a value between 40 and 50 pg/mL. Four additional subjects had at least two consecutive elevations of estradiol (range 43-240 pg/mL) levels during the 12-week dosing interval, but there was no indication of luteal function for any of the subjects during this period.

Administration of LUPRON DEPOT 11.25 mg in therapeutic doses results in suppression of the pituitary-gonadal system. Normal function is usually restored within three months after treatment is discontinued. Therefore, diagnostic tests of pituitary gonadotropic and gonadal functions conducted during treatment and for up to three months after discontinuation of LUPRON DEPOT 11.25 mg may be affected.

12.3 Pharmacokinetics

Absorption

Following a single injection of the 3-month formulation of LUPRON DEPOT 11.25 mg in female subjects, a mean plasma leuprolide concentration of 36.3 ng/mL was observed at 4 hours. Leuprolide appeared to be released at a constant rate following the onset of steady-state levels during the third week after dosing and mean levels then declined gradually to near the lower limit of detection by 12 weeks. The mean (± standard deviation) leuprolide concentration from 3 to 12 weeks was 0.23 ± 0.09 ng/mL. However, intact leuprolide and an inactive major metabolite could not be distinguished by the assay which was employed in the study. The initial burst, followed by the rapid decline to a steady-state level, was similar to the release pattern seen with the monthly formulation.

In a pharmacokinetic/pharmacodynamic study of endometriosis patients, IM LUPRON DEPOT 11.25 mg (n=19) every 12 weeks or IM LUPRON DEPOT 3.75 mg (n=15) every 4 weeks was administered for 24 weeks. There was no statistically significant difference in changes of serum estradiol concentration from baseline between the 2 treatment groups.

Distribution

The mean steady-state volume of distribution of leuprolide following intravenous bolus administration to healthy male volunteers was 27 L. In vitro binding to human plasma proteins ranged from 43% to 49%.

Metabolism

Leuprolide acetate is a peptide that is primarily degraded by peptidase. In healthy male volunteers, a 1 mg bolus of leuprolide administered intravenously revealed that the mean systemic clearance was 7.6 L/h, with a terminal elimination half-life of approximately 3 hours based on a two-compartment model.

Metabolite I, a smaller inactive peptide, plasma concentrations measured in 5 prostate cancer patients reached maximum concentration 2 to 6 hours after dosing and were approximately 6% of the peak parent drug concentration. One week after dosing, mean plasma M-I concentrations were approximately 20% of mean leuprolide concentrations.

Excretion

Following administration of LUPRON DEPOT 3.75 mg to 3 patients, less than 5% of the dose was recovered as parent and M-I metabolite in the urine.

Use in Specific Populations

The pharmacokinetics of LUPRON DEPOT have not been evaluated in patients with hepatic and renal impairment.

Drug Interactions

No pharmacokinetic drug-drug interaction studies have been conducted with LUPRON DEPOT 11.25 mg. However, leuprolide acetate is a peptide that is not degraded by cytochrome P-450 enzymes; hence, drug interactions associated with cytochrome P-450 enzymes would not be expected to occur.

13 NONCLINICAL TOXICOLOGY

13.1 Carcinogenesis, Mutagenesis, Impairment of Fertility

A two-year carcinogenicity study was conducted in rats and mice. In rats, a dose-related increase of benign pituitary hyperplasia and benign pituitary adenomas was noted at 24 months when the drug was administered subcutaneously at high daily doses (0.6 to 4 mg/kg). There was a significant but not dose-related increase of pancreatic islet-cell adenomas in females and of testicular interstitial cell adenomas in males (highest incidence in the low dose group). In mice, no leuprolide acetate-induced tumors or pituitary abnormalities were observed at a dose as high as 60 mg/kg for two years. Patients have been treated with leuprolide acetate for up to three years with doses as high as 10 mg/day and for two years with doses as high as 20 mg/day without demonstrable pituitary abnormalities.

Mutagenicity studies have been performed with leuprolide acetate using bacterial and mammalian systems. These studies provided no evidence of a mutagenic potential.

14 CLINICAL STUDIES

The safety and efficacy of LUPRON DEPOT 11.25 mg for the indicated populations has been established based on adequate and well-controlled studies in adults (See Table 8) of LUPRON DEPOT 3.75 mg and on a single trial of LUPRON DEPOT 11.25 mg [see Indications and Usage (1)].

14.1 Endometriosis

LUPRON DEPOT 11.25 mg Monotherapy

In controlled clinical studies, LUPRON DEPOT 3.75 mg monthly for six months was shown to be comparable to danazol 800 mg/day in relieving the clinical sign/symptoms of endometriosis (pelvic pain, dysmenorrhea, dyspareunia, pelvic tenderness, and induration) and in reducing the size of endometrial implants as evidenced by laparoscopy.

The clinical significance of a decrease in endometriotic lesions is not known, and laparoscopic staging of endometriosis does not necessarily correlate with the severity of symptoms.

LUPRON DEPOT 3.75 mg monthly induced amenorrhea in 74% and 98% of the women after the first and second month of treatment, respectively. Most of the remaining women reported episodes of only light bleeding or spotting. In the first, second and third post-treatment months, normal menstrual cycles resumed in 7%, 71% and 95% of women, respectively, excluding those who became pregnant.

Figure 1 illustrates the percent of women with symptoms at baseline, final treatment visit and sustained relief at 6 and 12 months following discontinuation of treatment for the various symptoms evaluated during the two controlled clinical studies. A total of 166 women received LUPRON DEPOT 3.75 mg. Seventy-five percent (N=125) of these elected to participate in the follow-up period. Of these women, 36% and 24% are included in the 6-month and 12-month follow-up analysis, respectively. All the women who had a pain evaluation at baseline and at least of one treatment visit are included in the Baseline (B) and final treatment visit (F) analysis.

Figure 1. Percent of Women with Signs/Symptoms of Endometriosis at Baseline, Final Treatment Visit, and After 6 and 12 Months of Follow-Up, LUPRON DEPOT 3.75 mg Monthly for Six Months

In a pharmacokinetic/pharmacodynamic study of healthy female subjects (N=20) LUPRON DEPOT 11.25 mg induced amenorrhea in 85% (N=17) of subjects during the initial month and 100% during the second month following the injection. All subjects remained amenorrheic through the remainder of the 12-week dosing interval. Episodes of light bleeding and spotting were reported by a majority of subjects during the first month after the injection and in a few subjects at later time-points. Menses resumed on average 12 weeks (range 2.9 to 20.4 weeks) following the end of the 12-week dosing interval.

LUPRON DEPOT 11.25 mg produced similar pharmacodynamic effects in terms of hormonal and menstrual suppression to those achieved with monthly injections of LUPRON DEPOT 3.75 mg during the controlled clinical trials for the management of endometriosis and the anemia caused by uterine fibroids [see Clinical Pharmacology (12.2)].

A six-month pharmacokinetic/pharmacodynamic post-marketing study in 41 women that included both the LUPRON DEPOT 3.75 mg dose (N=20) administered once monthly and the LUPRON DEPOT 11.25 mg dose (N=21) administered once every three months did not reveal clinically significant differences in terms of efficacy in reducing painful symptoms of endometriosis or magnitude of the decrease in bone mineral density (BMD) associated with use of LUPRON DEPOT 3.75 mg and LUPRON DEPOT 11.25 mg. In both treatment groups, suppression of menses (defined as no new menses for at least 60 consecutive days) was achieved in 100% of the women who remained in the study for at least 60 days. Vertebral bone density measured by dual energy x-ray absorptiometry (DEXA) decreased compared with baseline by an average of 3.0% and 2.8% at six months for the two groups, respectively.

LUPRON DEPOT with Norethindrone Acetate Add-Back Therapy

Two clinical studies with treatment duration of 12 months were conducted to evaluate the effect of co-administration of LUPRON DEPOT 3.75 mg and norethindrone acetate on the loss of bone mineral density (BMD) associated with LUPRON DEPOT 3.75 mg and on the efficacy of LUPRON DEPOT in relieving symptoms of endometriosis. All women in these studies received calcium supplementation with 1000 mg elemental calcium. A total of 242 women were treated with monthly administration of LUPRON DEPOT 3.75 mg (13 injections) and 191 of them were co-administered 5 mg norethindrone acetate taken daily. The population age range was 17-43 years old. The majority of women were Caucasian (87%).

One co-administration study was a controlled, randomized and double-blind study included 51 women treated monthly with LUPRON DEPOT 3.75 mg alone and 55 women treated monthly with LUPRON DEPOT 3.75 mg plus norethindrone acetate daily. Women in this trial were followed for up to 24 months after completing one year of treatment. The other study was an open-label single arm clinical study in 136 women of one year of treatment with LUPRON DEPOT 3.75 mg monthly and daily norethindrone acetate 5 mg, with follow-up for up to 12 months after completing treatment. See Table 8.

The assessment of efficacy was based on the investigator's or the woman’s monthly assessment of five signs or symptoms of endometriosis (dysmenorrhea, pelvic pain, deep dyspareunia, pelvic tenderness and pelvic induration).

Table 8 below provides detailed efficacy data regarding relief of symptoms of endometriosis based on the two studies of co-administration of LUPRON DEPOT 3.75 mg monthly and norethindrone acetate 5 mg daily.

Table 8. Effect of LUPRON DEPOT and Norethindrone Acetate on the Symptoms of Endometriosis and Mean Clinical Severity Scores
 |  |  | Percent of Women with Symptoms |  |  | Clinical Pain Severity Score
 |  |  | Baseline |  | Final | Baseline |  | Final
Variable | Study | Group | N^1 | (%)^2 | (%) | N^1 | Value^3 | Change
 | Controlled Study | LD*^4 | 51 | (100) | (4) | 50 | 3.2 | -2.0
Dysmenorrhea |  | LD/N† | 55 | (100) | (4) | 54 | 3.1 | -2.0
 | Open Label Study | LD/N^5 | 136 | (99) | (9) | 134 | 3.3 | -2.1
 | Controlled Study | LD^4 | 51 | (100) | (66) | 50 | 2.9 | -1.1
Pelvic Pain |  | LD/N | 55 | (96) | (56) | 54 | 3.1 | -1.1
 | Open Label Study | LD/N^5 | 136 | (99) | (63) | 134 | 3.2 | -1.2
 | Controlled Study | LD | 42 | (83) | (37) | 25 | 2.4 | -1.0
Deep Dyspareunia |  | LD/N | 43 | (84) | (45) | 30 | 2.7 | -0.8
 | Open Label Study | LD/N | 102 | (91) | (53) | 94 | 2.7 | -1.0
 | Controlled Study | LD^4 | 51 | (94) | (34) | 50 | 2.5 | -1.0
Pelvic Tenderness |  | LD/N | 54 | (91) | (34) | 52 | 2.6 | -0.9
 | Open Label Study | LD/N^5 | 136 | (99) | (39) | 134 | 2.9 | -1.4
 | Controlled Study | LD^4 | 51 | (51) | (12) | 50 | 1.9 | -0.4
Pelvic Induration |  | LD/N | 54 | (46) | (17) | 52 | 1.6 | -0.4
 | Open Label Study | LD/N^5 | 136 | (75) | (21) | 134 | 2.2 | -0.9
* LD = LUPRON DEPOT 3.75 mg assessment
† LD/N = LUPRON DEPOT 3.75 mg plus norethindrone acetate 5 mg
^1 Number of women that were included in the assessment
^2 Percentage of women with the symptom/sign
^3 Value description: 1 = none; 2 = mild; 3 = moderate; 4 = severe
^4 6-month study duration of treatment
^5 12-month study duration of treatment with 12 months of follow up

Suppression of menses (menses was defined as three or more consecutive days of menstrual bleeding) was maintained throughout treatment in 84% and 73% of women receiving leuprolide acetate and norethindrone acetate, in the controlled study and open label study, respectively. The median time for menses resumption after treatment with leuprolide acetate and norethindrone acetate was 8 weeks.

Changes in Bone Density

The effect of LUPRON DEPOT 3.75 mg and norethindrone acetate on bone mineral density was evaluated by dual energy x-ray absorptiometry (DEXA) scan in the two clinical trials. For the open-label study, success in mitigating BMD loss was defined as the lower bound of the 95% confidence interval around the change from baseline at one year of treatment not to exceed -2.2%. The bone mineral density data of the lumbar spine from these two studies are presented in Table 9.

Table 9. Mean Percent Change from Baseline in Bone Mineral Density of Lumbar Spine
 | LUPRON DEPOT 3.75 mg (LD only) |  | LUPRON DEPOT 3.75 mg plus norethindrone acetate 5 mg daily (LD/N)
 | Controlled Study |  | Controlled Study |  | Open Label Study
 | N | Change Mean (95% CI)# | N | Change Mean (95% CI)# | N | Change Mean (95% CI)#
Week 24* | 41 | -3.2% (-3.8, -2.6) | 42 | -0.3% (-0.8, 0.3) | 115 | -0.2% (-0.6, 0.2)
Week 52† | 29 | -6.3% (-7.1, -5.4) | 32 | -1.0% (-1.9, -0.1) | 84 | -1.1% (-1.6, -0.5)
* Includes on-treatment measurements that fell within 2 to 252 days after the first day of treatment.
† Includes on-treatment measurements > 252 days after the first day of treatment.
# 95% CI: 95% Confidence Interval

The change in BMD following discontinuation of treatment is shown in Table 10.

Table 10. Mean Percent Change from Baseline in BMD of Lumbar Spine in Post-Treatment Follow-up Period^1
Post Treatment Measurement | Controlled Study |  |  |  |  |  | Open Label Study
 | LD-Only |  |  | LD/N |  |  | LD/N
 | N | Mean % Change | 95% CI (%)^2 | N | Mean % Change | 95% CI (%) | N | Mean % Change | 95% CI (%)^2
Month 8 | 19 | -3.3 | (-4.9, -1.8) | 23 | -0.9 | (-2.1, 0.4) | 89 | -0.6 | (-1.2, 0.0)
Month 12 | 16 | -2.2 | (-3.3, -1.1) | 12 | -0.7 | (-2.1, 0.6) | 65 | 0.1 | (-0.6, 0.7)
^1 Patients with post treatment measurements
^2 95% CI (2-sided) of percent change in BMD values from baseline

These clinical studies demonstrated that co-administration of leuprolide acetate and norethindrone acetate 5 mg daily is effective in significantly reducing the loss of bone mineral density that occurs with both LUPRON DEPOT 3.75 mg and 11.25 mg treatments, and in relieving symptoms of endometriosis.

14.2 Fibroids

LUPRON DEPOT 3.75 mg monthly for a period of three to six months was studied in four controlled clinical trials.

In one of these clinical studies, enrollment was based on hematocrit ≤ 30% and/or hemoglobin ≤ 10.2 g/dL. Administration of LUPRON DEPOT 3.75 mg monthly, concomitantly with iron, produced an increase of ≥ 6% hematocrit and ≥ 2 g/dL hemoglobin in 77% of women at three months of therapy. The mean change in hematocrit was 10.1% and the mean change in hemoglobin was 4.2 g/dL. Clinical response was judged to be a hematocrit of ≥ 36% and hemoglobin of ≥ 12 g/dL, thus allowing for autologous blood donation prior to surgery. At two and three months, respectively, 71% and 75% of women met this criterion (Table 11). These data suggest however, that some women may benefit from iron alone or 1 to 2 months of LUPRON DEPOT 3.75 mg.

Table 11. Percent of Women Achieving Hematocrit ≥ 36% and Hemoglobin ≥ 12 g/dL
Treatment Group | Week 4 | Week 8 | Week 12
LUPRON DEPOT 3.75 mg with Iron (N=104) | 40* | 71† | 75*
Iron Alone (N=98) | 17 | 39 | 49
* P-Value < 0.01
† P-Value < 0.001

Excessive vaginal bleeding (menorrhagia or menometrorrhagia) decreased in 80% of women at three months. Episodes of spotting and menstrual-like bleeding were noted in 16% of women at final visit.

In this same study, a decrease in uterine volume and myoma volume of ≥ 25% was seen in 60% and 54% of women, respectively. The mean fibroid diameter was 6.3 cm at pretreatment and decreased to 5.6 cm at the end of treatment. LUPRON DEPOT 3.75 mg was found to relieve symptoms of bloating, pelvic pain, and pressure.

In three other controlled clinical trials, enrollment was not based on hematologic status. Mean uterine volume decreased by 41% and myoma volume decreased by 37% at final visit as evidenced by ultrasound or MRI. The mean fibroid diameter was 5.6 cm at pretreatment and decreased to 4.7 cm at the end of treatment. These women also experienced a decrease in symptoms including excessive vaginal bleeding and pelvic discomfort. Ninety-five percent of these women became amenorrheic with 61%, 25%, and 4% experiencing amenorrhea during the first, second, and third treatment months respectively.

In addition, post-treatment follow-up was carried out in one clinical trial for a small percentage of women on LUPRON DEPOT 3.75 mg (N=46) among the 77% who demonstrated a ≥ 25% decrease in uterine volume while on therapy. Menses usually returned within two months of cessation of therapy. Mean time to return to pretreatment uterine size was 8.3 months. Regrowth did not appear to be related to pretreatment uterine volume.

Changes in Bone Density

In one of the studies for fibroids described above, when LUPRON DEPOT 3.75 mg was administered for three months in uterine fibroid women, vertebral trabecular bone mineral density as assessed by quantitative digital radiography (QDR) revealed a mean decrease of 2.7% compared with baseline. Six months after discontinuation of therapy, a trend toward recovery was observed.

16 HOW SUPPLIED/STORAGE AND HANDLING

Each LUPRON DEPOT 11.25 mg kit (NDC 0074-3663-03) contains:

- one prefilled dual-chamber syringe
- one plunger
- two alcohol swabs

Each single-dose dual chamber syringe contains sterile white lyophilized microsphere powder of 11.25 mg of leuprolide acetate incorporated in a biodegradable polymer in one chamber and a colorless diluent (1.5 mL) in the other chamber. When mixed with the diluent, LUPRON DEPOT 11.25 mg for injection, is administered as a single IM injection.

Store between 20° to 25°C (68° to 77°F). Excursions permitted to 15° to 30°C (59° to 86°F) [see USP Controlled Room Temperature].

17 PATIENT COUNSELING INFORMATION

Loss of Bone Density

Advise patients about the risk of loss of bone mineral density and that treatment is limited [see Dosage and Administration (2.1)]. Advise patients about other factors that can increase and decrease their risk of bone mineral density loss [see Warnings and Precautions (5.1)].

Embryo-Fetal Toxicity

- Advise females of reproductive potential of the possible risk to a fetus. Advise patients to inform healthcare provider of a known or suspected pregnancy [see Warnings and Precautions (5.2) and Use in Special Populations (8.1)].
- If contraception is indicated, advise females of reproductive potential to use non-hormonal contraception during treatment with LUPRON DEPOT 11.25 mg [see Use in Special Populations (8.3)].

Severe Cutaneous Adverse Reactions

Inform patients that severe cutaneous adverse reactions (SCARs), may occur during treatment with LUPRON DEPOT 11.25 mg. Advise patients to discontinue LUPRON DEPOT 11.25 mg and to immediately contact their healthcare provider if they experience signs or symptoms of SCARs [see Warnings and Precautions (5.3)].

Hypersensitivity Reactions

Inform patients that hypersensitivity reactions, including anaphylaxis, have been reported with LUPRON DEPOT. Advise patients to seek appropriate medical care if symptoms of hypersensitivity reactions occur [see Warnings and Precautions (5.4) and Adverse Reactions (6.2)].

Initial Flare of Symptoms

Advise patients that they may experience an increase in symptoms during the initial days of therapy. Advise patients that these symptoms should dissipate with continued therapy [see Warnings and Precautions (5.5)].

Convulsions

Inform patients that convulsions have been reported in patients who have received LUPRON DEPOT. Advise patients to seek medical attention in the event of a convulsion [see Warnings and Precautions (5.6)].

Clinical Depression

Inform patients that depression may occur or worsen during treatment with GnRH agonists, including LUPRON DEPOT 11.25 mg, especially in patients with a history of depression. Advise patients to immediately report thoughts and behaviors of concern to healthcare providers [see Warnings and Precautions (5.7)].

Manufactured for

AbbVie Inc.

North Chicago, IL 60064

by Takeda Pharmaceutical Company Limited

Osaka, Japan 540-8645

Revised 09/2025

20085415

PACKAGE LABEL

NDC 0074-3663-03

FOR ADULT USE 11.25 mg for 3-Month administration

Single Dose Administration Kit with prefilled dual-chamber syringe.

LupronDepot®

(leuprolide acetate for depot suspension)

11.25 mg for 3-Month administration

FOR INTRAMUSCULAR INJECTION

The front chamber contains: leuprolide acetate 11.25 mg, polylactic acid 99.3 mg, D-mannitol 19.45 mg

The second chamber contains: D-mannitol 75.0 mg, carboxymethylcellulose sodium 7.5 mg, polysorbate 80 1.5 mg, water for injection, USP, and glacial acetic acid, USP to control pH

Rx only